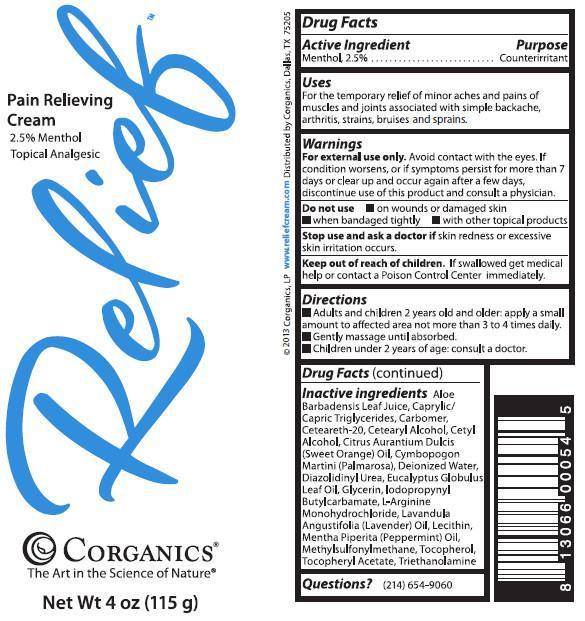 DRUG LABEL: Relief Pain Relieving Cream
NDC: 58559-001 | Form: CREAM
Manufacturer: Corganics, LP
Category: otc | Type: HUMAN OTC DRUG LABEL
Date: 20260114

ACTIVE INGREDIENTS: MENTHOL 2.5 g/100 g
INACTIVE INGREDIENTS: ALOE; CAPRYLIC/CAPRIC/LAURIC TRIGLYCERIDE; CARBOMER COPOLYMER TYPE A; POLYOXYL 20 CETOSTEARYL ETHER; CETOSTEARYL ALCOHOL; CETYL ALCOHOL; ORANGE OIL; PALMAROSA OIL; DIAZOLIDINYL UREA; WATER; EUCALYPTUS OIL; GLYCERIN; ARGININE; LAVENDER OIL; HYDROGENATED SOYBEAN LECITHIN; DIMETHYL SULFONE; PEPPERMINT OIL; TOCOPHEROL; .ALPHA.-TOCOPHEROL ACETATE; TROLAMINE

DRUG FACTS

ACTIVE INGREDIENT

Menthol 2.5%

PURPOSE

Counterirritant

USAGE

For the temporary Relief of pain of minor aches and pains of muscles and joints associated with simple backache, arthritis, strains, bruises and sprains.

WARNINGS

For external use only.If condition worsens, or if symptons persist for more than 7 days or clear up and occur again in a few days, discontinue use of this product and consult a physician.

Do Not Use

- on wounds or damaged skin
- when bandaged tightly
- with other topical products

Keep out of reach of children. If swallowed get medical help or contact a Poison Control Center immediately.

DIRECTIONS

- Adults and children 2 years old and older: apply a small amount to affected area not more than 3 to 4 times daily.
- Gently massage until absorbed.
- Children under 2 years of age: consult a doctor.

INACTIVE INGREDIENTS

Aloe Barbadensis Leaf Juice, Caprylic/Capric Triglycerides, Carbomer, Ceteareth-20, Cetearyl Alcohol, Cetyl Alcohol, Citrus Aurantium Dulcis (Sweet Orange) Oil, Cymbopogon Martini (Palmarosa) Oil, Deionized Water, Diazolidinyl Urea, Eucalyptus Globulus Leaf Oil, Glycerine, Iodopropynyl Butylcarbamate, L-Arginine, Lavandula Angustifolia (Lavender) Oil, Lecithin, Mentha Piperita (Peppermint Oil), Tocopherol, Methylsulfonylmethane, Tocopheryl Acetate, Triethanolamine